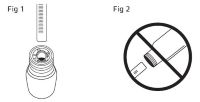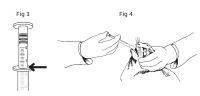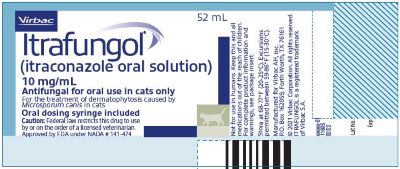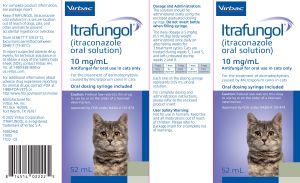 DRUG LABEL: Itrafungol
NDC: 51311-148 | Form: INJECTION, SOLUTION
Manufacturer: Virbac AH, Inc
Category: animal | Type: PRESCRIPTION ANIMAL DRUG LABEL
Date: 20230914

ACTIVE INGREDIENTS: itraconazole 10 mg/1 mL
INACTIVE INGREDIENTS: Saccharin sodium

Itrafungol®
(itraconazole oral solution)

GENERAL PRECAUTIONS

10 mg/mL
Antifungal for oral use in cats only

Caution

Federal law restricts this drug to use by or on the order of a licensed veterinarian.

Description

ITRAFUNGOL® (itraconazole oral solution) is a yellow to slightly amber, clear solution containing the active ingredient, itraconazole, at 10 mg/mL.

Indication

ITRAFUNGOL oral solution is indicated for the treatment of dermatophytosis caused by Microsporum canis in cats.

Dosage and Administration

The solution should be administered orally using the enclosed graduated dosing syringe.

The daily dosage is 5 mg/kg (0.5 mL/kg) body weight administered once daily on alternating weeks for 3 treatment cycles. Cats are treated during weeks 1, 3, and 5, and left untreated during weeks 2 and 4.

7 days | 7 days | 7 days | 7 days | 7 days
Daily treatment | No treatment | Daily treatment | No treatment | Daily treatment

Each line on the dosing syringe represents 0.05 mL of oral solution.

Table 1: Dose Table for ITRAFUNGOL
Weight of Cat | Volume of ITRAFUNGOL
0.5 lb | 0.1 mL
1.0 lb | 0.2 mL
1.5 lb | 0.35 mL
2.0 lb | 0.45 mL
2.5 lb | 0.55 mL
3.0 lb | 0.7 mL
3.5 lb | 0.8 mL
4.0 lb | 0.9 mL
4.5 lb | 1.0 mL
5.0 lb | 1.15 mL
6.0 lb | 1.35 mL
7.0 lb | 1.6 mL
8.0 lb | 1.8 mL
9.0 lb | 2.0 mL
10.0 lb | 2.25 mL
11.0 lb | 2.5 mL
12.0 lb | 2.7 mL
13.0 lb | 3.0 mL

The solution should be administered orally using the enclosed graduated dosing syringe. Keep the bottle upright and insert the dosing syringe through the opening of the top of the bottle (Figure 1). Do not invert the bottle (Figure 2). Fill the syringe by pulling the plunger until it reaches the graduation corresponding to the correct mL dose as indicated at the top of the syringe ring (Figure 3). Treat the cat by slowly and gently administering the liquid into the mouth, allowing the cat to swallow the product (Figure 4). For cats weighing more than 13.0 lbs, the total dose will need to be calculated and given over two doses as the dosing syringe only holds 3.0 mL of solution.

After dosing, do not replace syringe in the bottle. Rinse and dry the syringe. The bottle cap should be screwed back on tightly.

Contraindications

Do not administer to cats with hypersensitivity to itraconazole.

Warnings User Safety Warnings

Not for use in humans. Keep this and all medications out of reach of children. Wash hands and exposed skin after use. In case of accidental contact with eyes, rinse thoroughly with water. In case of pain or irritation, seek medical advice. In case of accidental ingestion, rinse mouth with water and seek medical advice.

Special precautions for person administering the veterinary product to the animal:

Microsporum canis dermatophytosis is a zoonotic disease (a disease that can be transmitted from animals to humans); therefore consult a physician if a suspected lesion occurs on a human. Wear protective gloves when handling the animal during treatment or when cleaning the syringe. Wash hands and exposed skin after handling the animal.

ITRAFUNGOL (itraconazole oral solution) has not been shown to be sporicidal; therefore in order to reduce zoonotic potential, environmental contamination, and to decrease course of the disease, topical and environmental treatment should also be utilized.

Animal Safety Warnings

ITRAFUNGOL oral solution has not been shown to be safe in pregnant cats (see Animal Safety). ITRAFUNGOL oral solution should only be used in pregnant or lactating cats when the benefits outweigh the potential risks.

Keep ITRAFUNGOL oral solution in a secure location out of reach of dogs, cats, and other animals to prevent accidental ingestion or overdose.

Precautions

In the laboratory effectiveness study, adverse reactions related to exposure to ITRAFUNGOL oral solution were primarily related to the gastrointestinal tract. Two ITRAFUNGOL-treated cats experienced transient hypersalivation during the dosing period. Vomiting was observed in 5 ITRAFUNGOL-treated cats (12.5%) during the dosing period compared to four cats (10%) in the control group. Diarrhea was observed in 9 ITRAFUNGOL-treated cats (22.5%) during the dosing period as compared to 7 cats (17.5%) in the control group.
One ITRAFUNGOL-treated cat showed mild increases in alanine aminotransferase (ALT) and aspartate aminotransferase (AST) at the end of the dosing period. No related clinical signs were observed, and these values returned to normal by the end of the follow-up period. One cat in the ITRAFUNGOL-treated group was noted to have lip erythema and lip induration once during the study.

Adverse Reactions

Post-Approval Experience (2021)
The following adverse events are based on post-approval adverse drug experience reporting for ITRAFUNGOL (itraconazole oral solution). Not all adverse events are reported to FDA/CVM. It is not always possible to reliably estimate the adverse event frequency or establish a causal relationship to product exposure using these data.
The following adverse events reported in cats are listed in decreasing order of reporting frequency:
Anorexia, emesis, elevated liver enzymes, lethargy, weight loss, icterus, elevated total bilirubin, and diarrhea.
Death (including euthanasia) has been reported. Some of these deaths were associated with the adverse events reported above.

Post-Approval Experience (2021)

The following adverse events are based on post-approval adverse drug experience reporting for ITRAFUNGOL (itraconazole oral solution). Not all adverse events are reported to FDA/CVM. It is not always possible to reliably estimate the adverse event frequency or establish a causal relationship to product exposure using these data.

The following adverse events reported in cats are listed in decreasing order of reporting frequency:

Anorexia, emesis, elevated liver enzymes, lethargy, weight loss, icterus, elevated total bilirubin, and diarrhea.

Death (including euthanasia) has been reported. Some of these deaths were associated with the adverse events reported above.

Contact Information

To report suspected adverse drug events, for technical assistance or to obtain a copy of the Safety Data Sheet (SDS), contact Virbac AH, Inc. at 1-800-338-3659 or us.virbac.com. For additional information about adverse drug experience reporting for animal drugs, contact FDA at 1-888-FDA-VETS or http://www.fda.gov/reportanimalae

Clinical Pharmacology

The mode of action of itraconazole is based on its highly selective binding ability to fungal cytochrome p-450 iso-enzymes. This inhibits the synthesis of ergosterol and affects membrane-bound enzyme function and membrane permeability. This effect is irreversible and causes structural degeneration of the fungal organism.

Itraconazole was absorbed rapidly following oral administration of ITRAFUNGOL oral solution to laboratory cats. Compared to the fasted state, administration of ITRAFUNGOL oral solution with food results in slightly higher (1.3 fold) mean total itraconazole exposure (AUC), delay in median Tmax (Fed 4 hours vs. Fasted 2 hours) and significant decrease (approximately 0.55 fold) in maximum plasma concentration (Cmax). ITRAFUNGOL oral solution can be administered with or without food. Itraconazole oral solution binds extensively to plasma proteins (> 99%), and distributes well to tissues. More than 30 metabolites are formed. Hydroxy-itraconazole is the parent metabolite and has antifungal activity. Excretion is rapid and primarily via the feces.

In cats, a single oral dose of 5 mg/kg results in a Cmax of 0.525 μg/mL post dose at 2 hours (Tmax). The AUC0-24h is 5.09 µg·h/mL and the half-life in plasma is 12.1 hours. After repeated daily administration for seven days at 5 mg/kg/day, the Cmax is doubled (1.05 μg/mL), the AUC0-24h is increased 3-fold (15.4 µg·h/
mL) and the plasma half-life is increased to 36 hours.

In the therapeutic treatment schedule, itraconazole is almost completely cleared from plasma after each wash-out period. The hydroxy-itraconazole remains near or below the quantification limit in feline plasma after a single dose of itraconazole oral solution at 5 mg/kg. However, after repeated daily doses of itraconazole oral solution at 5 mg/kg for one week, the hydroxy-itraconazole Cmax of 0.059 µg/mL was reached at 2 hours (Tmax). Itraconazole concentrations in cat’s hair vary; an increase occurs during treatment to a median value of 3.0 μg/g (mean 5.2 μg/g) at the end of the third dosing week and concentrations drop slowly to 1.5 μg/g (mean 1.9 μg/g) at 14 days after final dosing. Concentrations of hydroxy-itraconazole in hair are insignificant

Effectiveness

Laboratory Study
Effectiveness was demonstrated using ITRAFUNGOL oral solution in a masked, placebo controlled laboratory study. Eighty cats were experimentally infected with Microsporum canis and treated with either ITRAFUNGOL oral solution or sterile water (control product) for the proposed therapeutic treatment schedule followed by a 4-week follow-up period. No topical therapy was used during this study. A statistical difference (P =0.0003) in mycological cure rate (defined as two consecutive negative mycological cultures) was demonstrated between cats treated with ITRAFUNGOL oral solution (24/40 or 60%) versus control (1/40 or 2.5%). Ninety percent of ITRAFUNGOL-treated cats (36/40) achieved at least one negative culture by the end of the study. Improvement was seen in inoculation site erythema and skin thickening by Day 7 and in crusts and scales by Day 14. By the end of the study, 98% of ITRAFUNGOL-treated cats had complete resolution of all clinical lesions, compared to 15% in the control group.

Wood’s lamp cure (defined as no fluorescence at the base and mid-shaft of the hair) in the ITRAFUNGOL-treated group (39/40 or 97.5%) was higher compared to the control group (6/40 or 15%). Itraconazole MICs indicative of susceptibility were obtained in M. canis isolates from the two cats unsuccessfully treated with ITRAFUNGOL oral solution.

Field Study
A masked, positive-controlled, multi-site field study was conducted in client-owned cats in Europe. In this study, 514 cats diagnosed with dermatophytosis were randomly administered itraconazole oral solution or an active control.

Cats received a daily dose of either itraconazole oral solution for three alternating weeks plus a placebo tablet once daily for 5 consecutive weeks, or a placebo solution for three alternating weeks plus the active control once daily for five weeks. Success was evaluated on clinical cure, which was noted with a complete resolution of all clinical lesions. Four weeks after the end of treatment, 175 (83%) out of 207 cats treated with itraconazole oral solution were clinically cured.

Animal Safety

Margin of Safety Study with Recovery

In a margin of safety study, ITRAFUNGOL (itraconazole oral solution) was administered orally to 9-10 week old healthy kittens once daily at 0X (saline control), 1X (5 mg/kg), 3X (15 mg/kg), and 5X (25 mg/kg) the therapeutic dose for 17 alternating weeks (9 total weeks of dosing) followed by an 8 week recovery period. Hypersalivation during or immediately following dosing, vomiting, and loose stool were the most frequent abnormal clinical observations related to treatment with ITRAFUNGOL oral solution. Hypersalivation was limited to the 3X and 5X groups and was observed in every dosing cycle. Vomiting was noted at similar levels in the control, 1X and 3X groups; however, it occurred approximately twice as often in the 5X group. Mild gingival bleeding and perioral irritation (patchy alopecia and erythema) was noted in cats in the 3X and 5X groups. Food consumption was consistently higher throughout the study in the control group than the ITRAFUNGOL oral solution groups. The control group gained more weight during the study than the groups administered ITRAFUNGOL oral solution. Mild elevations in ALT were sporadically noted in all groups; however, the number of affected cats increased with the higher doses (two cats in the control group, two cats in the 1X group, three cats in the 3X group, and four cats in the 5X group). In most cats, ALT values peaked just above the upper limit of the reference range and were continuing to trend upward or were elevated yet stable at the end of the study. One cat in the 5X group exhibited inappetence progressing to anorexia, dehydration and vomiting during the first dosing cycle. This cat had repeated episodes of inappetence during the second and third dosing cycles. This cat also had markedly elevated ALT and AST values on Day 36 (693 U/L and 283 U/L, respectively), was treated with minimal supportive care and recovered to complete the study.

Margin of Safety Study

In a margin of safety study, ITRAFUNGOL oral solution was administered orally to healthy adult cats once daily at 0X (saline control), 1X (5 mg/kg), 3X (15 mg/kg), and 5X (25 mg/kg) the therapeutic dose for 17 alternating weeks (9 total weeks of dosing) with no recovery period. Hypersalivation was the most frequent abnormal clinical observation related to treatment with ITRAFUNGOL oral solution and the incidence increased with the higher doses. One cat in group 4 (5X; Cat #26302) lost 22% of its body weight and had a number of episodes of vomiting, salivation, and anorexia during the treatment period. This cat also had renal lesions found on histopathology. Increasing trends were noted in ALT, AST, and creatinine values in some cats administered ITRAFUNGOL oral solution as compared to baseline values. Abnormal renal findings included proximal convoluted tubule acute degeneration in 3 cats in the 1X group and 3 cats in the 5X group; one 5X cat (cat #26302) also had proximal convoluted tubule marked pallor and focal mononuclear cell infiltration in the kidneys. In the lungs, one 3X group cat and five 5X cats had intra-alveolar foamy macrophages; five 5X group cats had intra-alveolar syncytial cells.
These histopathology findings are likely related to exposure to ITRAFUNGOL oral solution, specifically the vehicle component hydroxypropyl--cyclodextrin (HPCD). There were no corresponding adverse clinical effects noted on observation or on clinical pathology analysis. In addition, similar changes have been described in literature in other species exposed to HPCD and have been reported to be reversible.

Reproductive Safety

In a study of 16 pregnant queens administered itraconazole oral solution at 5 mg/kg bodyweight for a total of 21 days (7 days on alternate weeks) during gestation or lactation, there was a high frequency of fetal resorption (partial and total), abnormal fetuses, and abnormal maternal behaviors. Confounding factors, such as infectious disease (Chlamydia psittaci) in some cats made it difficult to establish a definitive relationship between administration of itraconazole and the abnormal findings. However, the results of this study reveal potential reproductive safety risks and do not support the safe use of ITRAFUNGOL oral solution in pregnant queens.

Storage conditions

Store at 68-77°F (20-25°C). Excursions permitted between 59-86°F (15-30°C).

How supplied

ITRAFUNGOL oral solution is available in a glass bottle containing 52 mL of oral solution, closed with a child resistant screw cap and packaged in a cardboard box that includes a package insert and a graduated dosing syringe.

Approved by FDA under NADA # 141-474
Manufactured for Virbac AH, Inc., P.O. Box 162059, Fort Worth, TX 76161
Version Date: February 2023
1608247E
© 2022 Virbac Corporation. All rights reserved.
ITRAFUNGOL is a registered trademark of Virbac S.A.